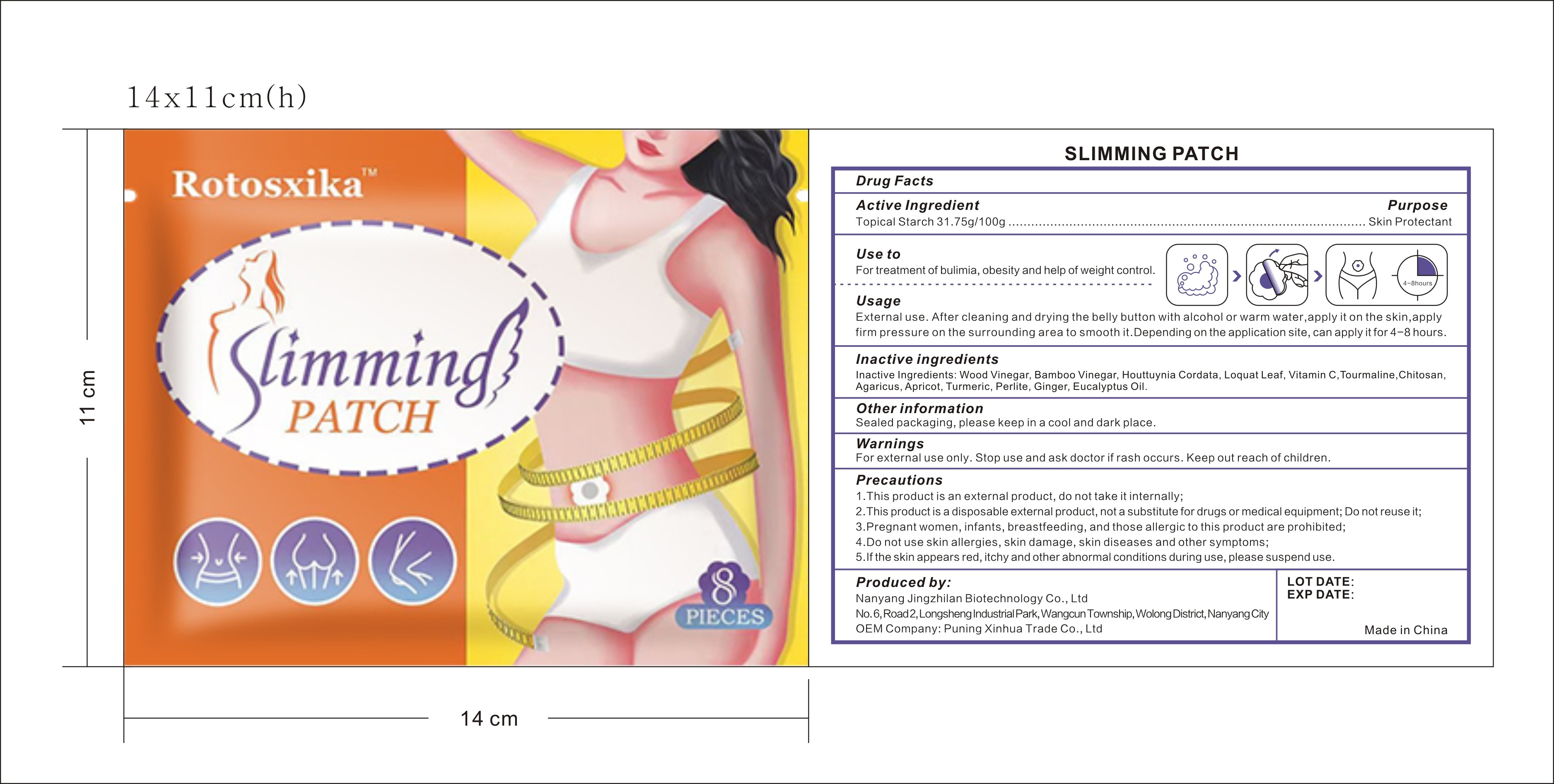 DRUG LABEL: Rotosxika SLIMMING patch
NDC: 83702-012 | Form: PATCH
Manufacturer: Puning Xinhua Trade Co., Ltd.
Category: otc | Type: HUMAN OTC DRUG LABEL
Date: 20231017

ACTIVE INGREDIENTS: STARCH, CORN 31.75 g/100 g
INACTIVE INGREDIENTS: HOUTTUYNIA CORDATA WHOLE; APRICOT; RHAPHIOLEPIS BIBAS LEAF; POLIGLUSAM; PYROLIGNEOUS ACID; TURMERIC; ASCORBIC ACID

Rotosxika SLIMMING PATCH

Active ingredient: Topical Starch 31.75g/100g

Purpose: Skin Protectant

INDICATIONS AND USAGE

Use to：For treatment of bulimia,obesity and help of weight control

DOSAGE AND ADMINISTRATION

Usage

External use.After cleaning and drying the belly button with alcohol or warm water,apply it on the skin,apply firm pressure on the surrounding area to smooth it.Depending on the application site,can apply it for 4-8 hours.

Warnings

For external use only.Stop use and ask doctor if rash occurs.Keep out reach of children.

Precautions

1. This product is an external product,do not take it internally;

2. This product is a disposable external product,not a substitute for drugs or medical equipment;Do not reuse it;

3. Pregnant women,infants,breastfeeding,and those allergic to this product are prohibited;

4. Do not use skin allergies,skin damage,skin diseases and other symptoms;

5. If the skin appears red,itchy and other abnormal conditions during use,please suspend use.

INACTIVE INGREDIENT

Inactive Ingredients: Wood Vinegar,Bamboo Vinegar, Houttuynia Cordata, Loquat Leaf,Vitamin C, Tourmaline,Chitosan,Agaricus,Apricot, Turmeric, Perlite,Ginger, Eucalyptus Oil.

Other information Sealed packaging,please keep in a cool and dark place.

Produced by:

Nanyang Jingzhilan Biotechnology Co., Ltd

No. 6, Road 2, Longsheng Industrial Park, Wangcun Township, Wolong District, Nanyang City

OEM Company: Puning Xinhua Trade Co., Ltd

Made in China

KEEP OUT OF REACH OF CHILDREN

Same as WARNINGS SECTION

see label